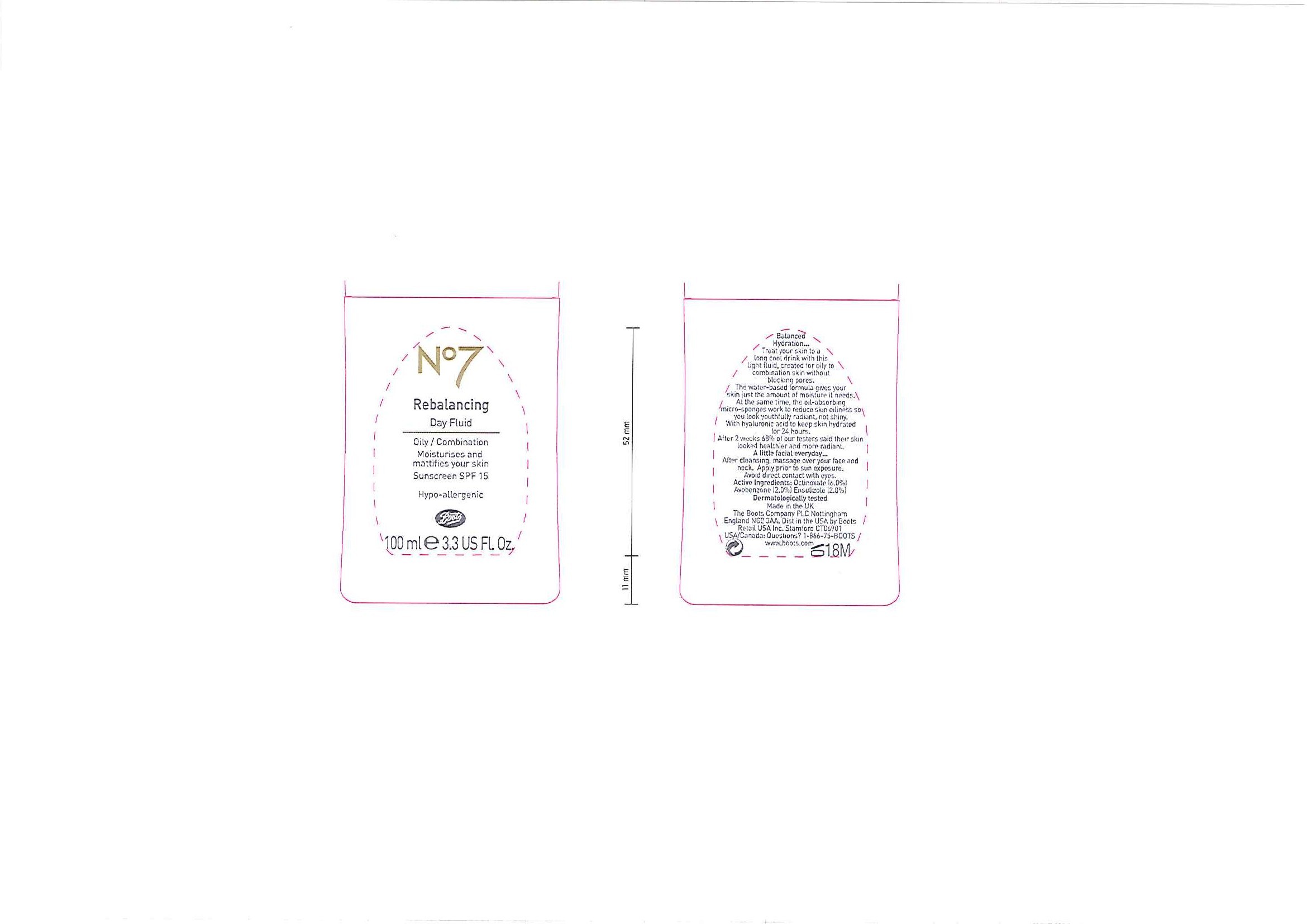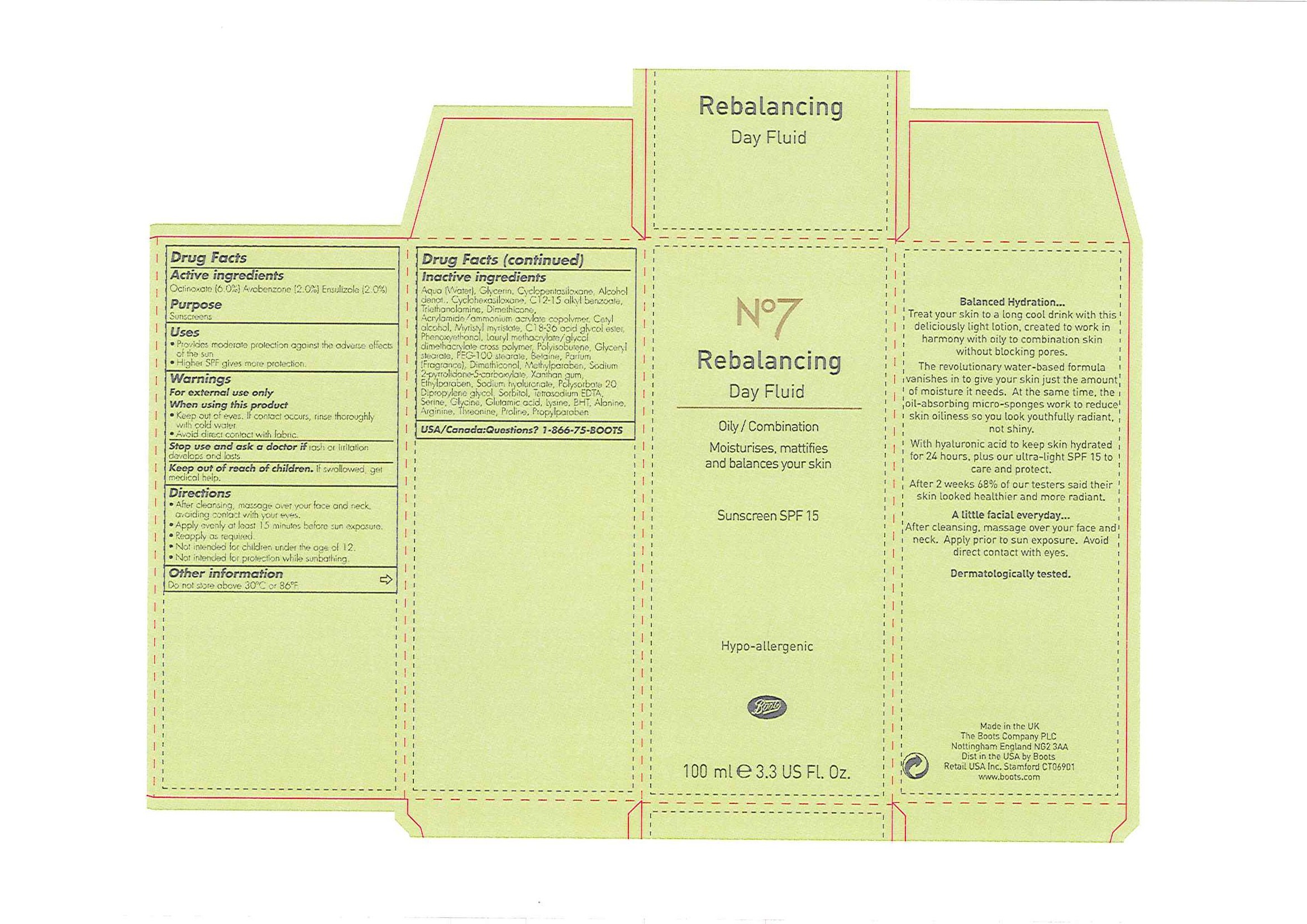 DRUG LABEL: No7 Rebalancing Day Fluid Sunscreen SPF 15
NDC: 11489-069 | Form: LOTION
Manufacturer: BCM Ltd
Category: otc | Type: HUMAN OTC DRUG LABEL
Date: 20101202

ACTIVE INGREDIENTS: OCTINOXATE 6 mL/100 mL; AVOBENZONE 2 mL/100 mL; ENSULIZOLE 2 mL/100 mL
INACTIVE INGREDIENTS: WATER; GLYCERIN; CYCLOMETHICONE 5; CYCLOMETHICONE 6; TROLAMINE; DIMETHICONE; CETYL ALCOHOL; PHENOXYETHANOL; GLYCERYL MONOSTEARATE; BETAINE; METHYLPARABEN; SODIUM PYRROLIDONE CARBOXYLATE; XANTHAN GUM; HYALURONATE SODIUM; ETHYLPARABEN; POLYSORBATE 20; SORBITOL; SERINE; GLYCINE; GLUTAMIC ACID; LYSINE; BUTYLATED HYDROXYTOLUENE; ALANINE; ARGININE; THREONINE; PROLINE; PROPYLPARABEN

Carton and bottle labelling

Active ingredients

Octinoxate (6.0%)

Avobenzone (2.0%)

Ensulizole (2.0%)

Purpose

Sunscreens

Uses

- Provides moderate protection against the adverse effects of the sun
- Higher SPF gives more protection

Warnings

For external use only

When using this product

- Keep out of eyes. If contact occurs, rinse thoroughly with cold water.
- Avoid direct contact with fabrics.

Stop use and ask a doctor if rash or irritation develops and lasts.

Keep out of reach of children. If swallowed, get medical help.

Directions

- After cleansing, massage over your face and neck, avoiding contact with your eyes.
- Apply evenly at least 15 minutes before sun exposure.
- Reapply as required.
- Not intended for children under the age of 12.
- Not intended for protection while sunbathing.

Other information

Do not store above 30^0C or 86^0F

Inactive ingredients

Aqua (Water), Glycerin, Cyclopentasiloxane, Alcohol denat., Cyclohexasiloxane, C12-15 alkyl benzoate, Triethanolamine, Dimethicone, Acrylamide/ammonium acrylate copolymer, Cetyl alcohol, Myristyl myristate, C18-36 acid glycol ester, Phenoxyethanol, Lauryl methacrylate/glycol dimethacrylate cross polymer, Polyisobutene, Glyceryl stearate, PEG-100 stearate, Betaine, Parfum (Fragrance), Dimethiconol, Methylparaben, Sodium 2-pyrrolidone-5-carboxylate, Xanthan gum, Ethylparaben, Sodium hyaluronate, Polysorbate 20, Dipropylene glycol, Sorbitol, Tetrasodium EDTA, Serine, Glycine, Glutamic acid, Lysine, BHT, Alanine, Arginine, Threonine, Propylparaben.

USA/Canada: Questions? 1-866-75-BOOTS

DESCRIPTION

Balanced Hydration...

Treat your skin to a long cool drink with this deliciously light lotion, created to work in harmony with oily to combination skin without blocking pores.

The revolutionary water-based formula vanishes in to give your skin just the amount of moisture it needs. At the same time, the oil-absorbing micro-sponges work to reduce skin oiliness so you look youthfully radiant, not shiny.

With hyaluronic acid to keep skin hydrated for 24 hours, plus our ultra-light SPF 15 to care and protect.

After 2 weeks 68% of our testers said their skin looked healthier and more radiant.

A little facial everyday...

After cleansing, massage over your face and neck. Apply prior to sun exposure. Avoid direct contact with eyes.

Dermatologically tested.

PATIENT COUNSELING INFORMATION

Made in the UK

The Boots Company PLC Nottingham England NG2 3AA

Dist in the USA by Boots Retail USA Inc. Stamford CT06901

www.boots.com

DESCRIPTION

Bottle label

Balanced Hydration...

Treat your skin to a long cool drink with this light fluid, created for oily to combination skin without blocking pores.

The water-based formula gives your skin just the amount of moisture it needs. At the same time, the oil-absorbing micro-sponges work to reduce skin oiliness so you look youthfully radiant, not shiny.

With hyaluronic acid to keep skin hydrated for 24 hours.

After 2 weeks 68% of our testers said their skin looked healthier and more radiant.

A little facial everyday...

After cleansing, massage over your face and neck.

Apply prior to sun exposure.

Avoid direct contact with eyes.

Dermatologically tested.

Active Ingredients:

Octinoxate (6.0%)

Avobenzone (2.0%)

Ensulizole (2.0%)

PATIENT COUNSELING INFORMATION

Made in the UK

The Boots Company PLC Nottingham England NG2 3AA.

Dist in the USA by Boots Retail USA Inc. Stamford CT06901

USA/Canada: Questions? 1-866-75-BOOTS

www.boots.com

Carton label

No7

Rebalancing Day Fluid

Oily/Combination

Moisturises, mattifies and balances your skin

Sunscreen SPF 15

Hypo-allergenic

Boots

100ml e 3.3 US Fl. Oz

Rebalancing Day Fluid carton.jpg

PACKAGE LABEL

No7 Rebalancing Day Fluid

Oily/Combination

Moisturises and mattifies your skin

Sunscreen SPF 15

Hypo-allergenic

Boots

100ml e 3.3 US Fl. Oz

Rebalancing Day Fluid bottle.jpg